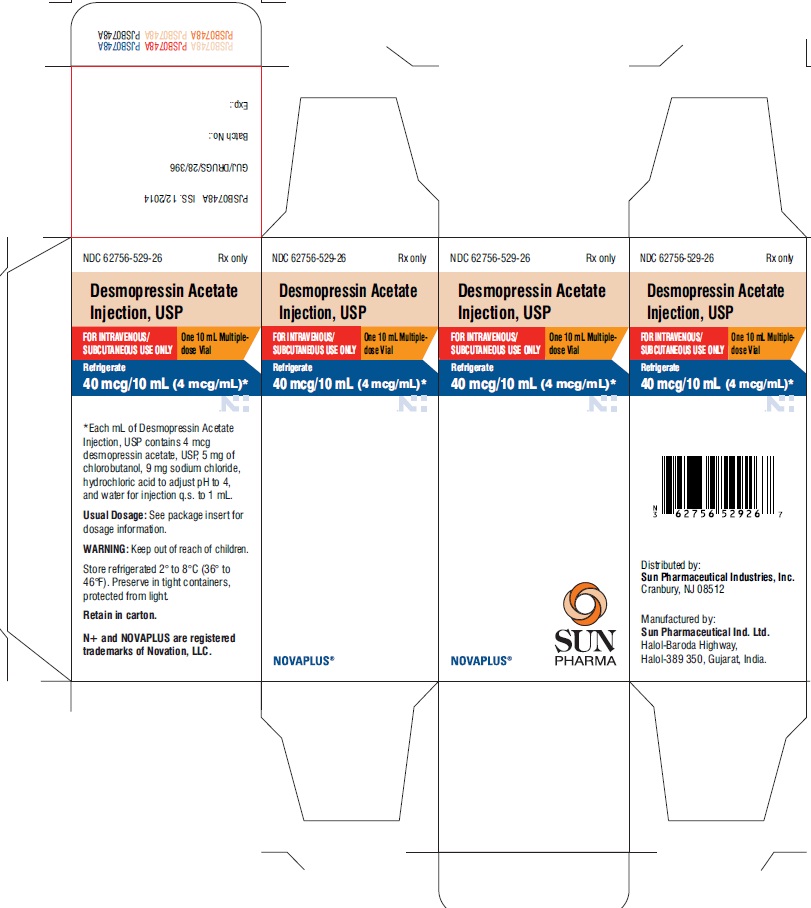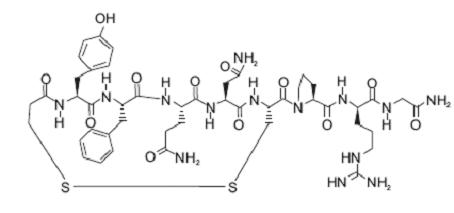 DRUG LABEL: desmopressin acetate
NDC: 62756-529 | Form: INJECTION, SOLUTION
Manufacturer: Sun Pharmaceutical Industries, Inc.
Category: prescription | Type: Human Prescription Drug Label
Date: 20200123

ACTIVE INGREDIENTS: DESMOPRESSIN ACETATE 4 ug/1 mL
INACTIVE INGREDIENTS: SODIUM CHLORIDE; HYDROCHLORIC ACID; CHLOROBUTANOL HEMIHYDRATE; WATER

Desmopressin Acetate Injection, USP, 4 mcg/mL

DESCRIPTION

Desmopressin acetate

injection, USP 4 mcg/mL is a synthetic analogue of the natural pituitary hormone 8-arginine vasopressin (ADH), an antidiuretic hormone affecting renal water conservation. It is chemically defined as follows:
Mol. Wt. 1069.23
Molecular Formula: C46H64N14O12S2

1-(3-mercaptopropionic acid)-8-D-arginine vasopressin acetate.
Desmopressin acetate

Injection, USP 4 mcg/mL is provided as a sterile, aqueous solution for injection.
Each mL provides:
Desmopressin acetate, USP, 4 mcg
Sodium chloride, 9 mg
Hydrochloric acid to adjust pH to 4
Water for injection, q.s. to 1 mL
The 10 mL vial contains chlorobutanol as a preservative (5 mg/mL).

CLINICAL PHARMACOLOGY

Desmopressin acetate

injection 4 mcg/mL contains as active substance, desmopressin acetate,USP, a synthetic analogue of the natural hormone arginine vasopressin. One mL (4 mcg) of desmopressin acetate solution has an antidiuretic activity of about 16 IU; 1 mcg of desmopressin acetate is equivalent to 4 IU.
Desmopressin acetate has been shown to be more potent than arginine vasopressin in increasing plasma levels of factor VIII activity in patients with hemophilia and von Willebrand’s disease Type I.
Dose-response studies were performed in healthy persons, using doses of 0.1 to 0.4 mcg/kg body weight, infused over a 10-minute period. Maximal dose response occurred at 0.3 to 0.4 mcg/kg. The response to desmopressin acetate of factor VIII activity and plasminogen activator is dose-related, with maximal plasma levels of 300 to 400 percent of initial concentrations obtained after infusion of 0.4 mcg/kg body weight. The increase is rapid and evident within 30 minutes, reaching a maximum at a point ranging from 90 minutes to two hours. The factor VIII related antigen and ristocetin cofactor activity were also increased to a smaller degree, but still are dose-dependent.

1. The biphasic half-lives of desmopressin acetate were 7.8 and 75.5 minutes for the fast and slow phases, respectively, compared with 2.5 and 14.5 minutes for lysine vasopressin, another form of the hormone. As a result, desmopressin acetate provides a prompt onset of antidiuretic action with a long duration after each administration.
2. The change in structure of arginine vasopressin to desmopressin acetate has resulted in a decreased vasopressor action and decreased actions on visceral smooth muscle relative to the enhanced antidiuretic activity, so that clinically effective antidiuretic doses are usually below threshold levels for effects on vascular or visceral smooth muscle.
3. When administered by injection, desmopressin acetate has an antidiuretic effect about ten times that of an equivalent dose administered intranasally.
4. The bioavailability of the subcutaneous route of administration was determined qualitatively using urine output data. The exact fraction of drug absorbed by that route of administration has not been quantitatively determined.
5. The percentage increase of factor VIII levels in patients with mild hemophilia A and von Willebrand’s disease was not significantly different from that observed in normal healthy individuals when treated with 0.3 mcg/kg of desmopressin acetate infused over 10 minutes.
6. Plasminogen activator activity increases rapidly after desmopressin acetate infusion, but there has been no clinically significant fibrinolysis in patients treated with desmopressin acetate.
7. The effect of repeated desmopressin acetate administration when doses were given every 12 to 24 hours has generally shown a gradual diminution of the factor VIII activity increase noted with a single dose. The initial response is reproducible in any particular patient if there are 2 or 3 days between administrations.

Human Pharmacokinetics: Desmopressin acetate is mainly excreted in the urine. A pharmacokinetic study conducted in healthy volunteers and patients with mild, moderate, and severe renal impairment (n=24, 6 subjects in each group) receiving single dose desmopressin acetate (2 mcg) injection demonstrated a difference in desmopressin acetate terminal half-life. Terminal half-life significantly increased from 3 hours in normal healthy patients to 9 hours in patients with severe renal impairment. (See CONTRAINDICATIONS.)

INDICATIONS AND USAGE

Hemophilia A: Desmopressin Acetate Injection 4 mcg/mL is indicated for patients with hemophilia A with factor VIII coagulant activity levels greater than 5%.
Desmopressin acetate injection will often maintain hemostasis in patients with hemophilia A during surgical procedures and postoperatively when administered 30 minutes prior to scheduled procedure.
Desmopressin acetate injection will also stop bleeding in hemophilia A patients with episodes of spontaneous or trauma-induced injuries such as hemarthroses, intramuscular hematomas or mucosal bleeding.

Desmopressin acetate injection is not indicated for the treatment of hemophilia A with factor VIII coagulant activity levels equal to or less than 5%, or for the treatment of hemophilia B, or in patients who have factor VIII antibodies.

In certain clinical situations, it may be justified to try desmopressin acetate injection in patients with factor VIII levels between 2% to 5%; however, these patients should be carefully monitored.
von Willebrand’s Disease (Type I): Desmopressin acetate injection 4 mcg/mL is indicated for patients with mild to moderate classic von Willebrand’s disease (Type I) with factor VIII levels greater than 5%. Desmopressin acetate injection will often maintain hemostasis in patients with mild to moderate von Willebrand’s disease during surgical procedures and postoperatively when administered 30 minutes prior to the scheduled procedure.
Desmopressin acetate injection will usually stop bleeding in mild to moderate von Willebrand’s patients with episodes of spontaneous or trauma-induced injuries such as hemarthroses, intramuscular hematomas or mucosal bleeding.
Those von Willebrand’s disease patients who are least likely to respond are those with severe homozygous von Willebrand’s disease with factor VIII coagulant activity and factor VIII von Willebrand factor antigen levels less than 1%. Other patients may respond in a variable fashion depending on the type of molecular defect they have. Bleeding time and factor VIII coagulant activity, ristocetin cofactor activity, and von Willebrand factor antigen should be checked during administration of desmopressin acetate injection to ensure that adequate levels are being achieved.
Desmopressin acetate injection is not indicated for the treatment of severe classic von Willebrand’s disease (Type I) and when there is evidence of an abnormal molecular form of factor VIII antigen. (See WARNINGS.)
Diabetes Insipidus: Desmopressin acetate injection 4 mcg/mL is indicated as antidiuretic replacement therapy in the management of central (cranial) diabetes insipidus and for the management of the temporary polyuria and polydipsia following head trauma or surgery in the pituitary region. Desmopressin acetate injection is ineffective for the treatment of nephrogenic diabetes insipidus.
Desmopressin acetate is also available as an intranasal preparation. However, this means of delivery can be compromised by a variety of factors that can make nasal insufflation ineffective or inappropriate. These include poor intranasal absorption, nasal congestion and blockage, nasal discharge, atrophy of nasal mucosa, and severe atrophic rhinitis. Intranasal delivery may be inappropriate where there is an impaired level of consciousness. In addition, cranial surgical procedures, such as transsphenoidal hypophysectomy, create situations where an alternative route of administration is needed as in cases of nasal packing or recovery from surgery.

CONTRAINDICATIONS

Desmopressin acetate injection 4 mcg/mL is contraindicated in individuals with known hypersensitivity to desmopressin acetate or to any of the components of desmopressin acetate injection 4 mcg/mL.
Desmopressin acetate injection is contraindicated in patients with moderate to severe renal impairment (defined as a creatinine clearance below 50 ml/min).
Desmopressin acetate injection is contraindicated in patients with hyponatremia or a history of hyponatremia.

WARNINGS

1. Very rare cases of hyponatremia have been reported from world-wide postmarketing experience in patients treated with desmopressin acetate. Desmopressin acetate is a potent antidiuretic which, when administered, may lead to water intoxication and/or hyponatremia. Unless properly diagnosed and treated hyponatremia can be fatal. Therefore, fluid restriction is recommended and should be discussed with the patient and/or guardian. Careful medical supervision is required.
2. When desmopressin acetate injection is administered to patients who do not have need of antidiuretic hormone for its antidiuretic effect, in particular in pediatric and geriatric patients, fluid intake should be adjusted downward to decrease the potential occurrence of water intoxication and hyponatremia. (See PRECAUTIONS, Pediatric Use and Geriatric Use.) All patients receiving desmopressin acetate therapy should be observed for the following signs of symptoms associated with hyponatremia: headache, nausea/vomiting, decreased serum sodium, weight gain, restlessness, fatigue, lethargy, disorientation, depressed reflexes, loss of appetite, irritability, muscle weakness, muscle spasms or cramps and abnormal mental status such as hallucinations, decreased consciousness and confusion. Severe symptoms may include one or a combination of the following: seizure, coma and/or respiratory arrest. Particular attention should be paid to the possibility of the rare occurrence of an extreme decrease in plasma osmolality that may result in seizures which could lead to coma.
3. Desmopressin acetate should not be used to treat patients with Type IIB von Willebrand’s disease since platelet aggregation may be induced.
4. Desmopressin acetate should be used with caution in patients with habitual or psychogenic polydipsia who may be more likely to drink excessive amounts of water, putting them at greater risk of hyponatremia.

PRECAUTIONS

General

For injection use only.
Desmopressin acetate injection 4 mcg/mL has infrequently produced changes in blood pressure causing either a slight elevation in blood pressure or a transient fall in blood pressure and a compensatory increase in heart rate. The drug should be used with caution in patients with coronary artery insufficiency and/or hypertensive cardiovascular disease.
Desmopressin acetate should be used with caution in patients with conditions associated with fluid and electrolyte imbalance, such as cystic fibrosis, heart failure and renal disorders, because these patients are prone to hyponatremia.
There have been rare reports of thrombotic events following desmopressin acetate injection 4 mcg/mL in patients predisposed to thrombus formation. No causality has been determined, however, the drug should be used with caution in these patients.
Severe allergic reactions have been reported rarely. Anaphylaxis has been reported rarely with intravenous and intranasal desmopressin acetate, including isolated cases of fatal anaphylaxis with intravenous desmopressin acetate. It is not known whether antibodies to desmopressin acetate injection 4 mcg/mL are produced after repeated injections.
Hemophilia A: Laboratory tests for assessing patient status include levels of factor VIII coagulant, factor VIII antigen and factor VIII ristocetin cofactor (von Willebrand factor) as well as activated partial thromboplastin time. Factor VIII coagulant activity should be determined before giving desmopressin acetate for hemostasis. If factor VIII coagulant activity is present at less than 5% of normal, desmopressin acetate should not be relied on.
von Willebrand’s Disease: Laboratory tests for assessing patient status include levels of factor VIII coagulant activity, factor VIII ristocetin cofactor activity, and factor VIII von Willebrand factor antigen. The skin bleeding time may be helpful in following these patients.
Diabetes Insipidus: Laboratory tests for monitoring the patient include urine volume and osmolality. In some cases, plasma osmolality may be required.

Drug Interactions

Although the pressor activity of desmopressin acetate is very low compared with the antidiuretic activity, use of doses as large as 0.3 mcg/kg of desmopressin acetate with other pressor agents should be done only with careful patient monitoring. The concomitant administration of drugs that may increase the risk of water intoxication with hyponatremia, (e.g., tricyclic antidepressants, selective serotonin re-uptake inhibitors, chlorpromazine, opiate analgesics, NSAIDs, lamotrigine and carbamazepine) should be performed with caution.
Desmopressin acetate has been used with epsilon aminocaproic acid without adverse effects.

Carcinogenicity, Mutagenicity, Impairment of Fertility

Studies with desmopressin acetate have not been performed to evaluate carcinogenic potential, mutagenic potential or effects on fertility.

Pregnancy Category B

Fertility studies have not been done. Teratology studies in rats and rabbits at doses from 0.05 to 10 mcg/kg/day (approximately 0.1 times the maximum systemic human exposure in rats and up to 38 times the maximum systemic human exposure in rabbits based on surface area, mg/m^2) revealed no harm to the fetus due to desmopressin acetate. There are, however, no adequate and well controlled studies in pregnant women. Because animal reproduction studies are not always predictive of human response, this drug should be used during pregnancy only if clearly needed.
Several publications of desmopressin acetate’s use in the management of diabetes insipidus during pregnancy are available; these include a few anecdotal reports of congenital anomalies and low birth weight babies. However, no causal connection between these events and desmopressin acetate has been established. A fifteen year, Swedish epidemiologic study of the use of desmopressin acetate in pregnant women with diabetes insipidus found the rate of birth defects to be no greater than that in the general population; however, the statistical power of this study is low. As opposed to preparations containing natural hormones, desmopressin acetate in antidiuretic doses has no uterotonic action and the physician will have to weigh the therapeutic advantages against the possible risks in each case.

Nursing Mothers

There have been no controlled studies in nursing mothers. A single study in postpartum women demonstrated a marked change in plasma, but little if any change in assayable desmopressin acetate in breast milk following an intranasal dose of 10 mcg. It is not known whether this drug is excreted in human milk. Because many drugs are excreted in human milk, caution should be exercised when desmopressin acetate is administered to a nursing woman.

Pediatric Use

Use in infants and pediatric patients will require careful fluid intake restriction to prevent possible hyponatremia and water intoxication. Fluid restriction should be discussed with the patient and/or guardian. (See WARNINGS.) Desmopressin acetate injection 4 mcg/mL should not be used in infants less than three months of age in the treatment of hemophilia A or von Willebrand’s disease; safety and effectiveness in pediatric patients under 12 years of age with diabetes insipidus have not been established.

Geriatric Use

Clinical studies of desmopressin acetate injection did not include sufficient numbers of subjects aged 65 and over to determine whether they respond differently from younger subjects. Other reported clinical experience has not identified differences in responses between the elderly and younger patients. In general, dose selection should be cautious, usually starting at the low end of the dosing range, reflecting the greater frequency of decreased hepatic, renal, or cardiac function, and of concomitant disease or other drug therapy.
This drug is known to be substantially excreted by the kidney, and the risk of toxic reactions to this drug may be greater in patients with impaired renal function. Because elderly patients are more likely to have decreased renal function, care should be taken in dose selection, and it may be useful to monitor renal function. Desmopressin acetate is contraindicated in patients with moderate to severe renal impairment (defined as a creatinine clearance below 50 ml/min). (See CLINICAL PHARMACOLOGY, Human Pharmacokinetics and CONTRAINDICATIONS.)
Use of desmopressin acetate injection in geriatric patients will require careful fluid intake restrictions to prevent possible hyponatremia and water intoxication. Fluid restriction should be discussed with the patient. (See WARNINGS.)

ADVERSE REACTIONS

Infrequently, desmopressin acetate has produced transient headache, nausea, mild abdominal cramps and vulval pain. These symptoms disappeared with reduction in dosage. Occasionally, injection of desmopressin acetate has produced local erythema, swelling or burning pain. Occasional facial flushing has been reported with the administration of desmopressin acetate. Desmopressin acetate injection has infrequently produced changes in blood pressure causing either a slight elevation or a transient fall and a compensatory increase in heart rate. Severe allergic reactions including anaphylaxis have been reported rarely with desmopressin acetate injection.
See WARNINGS for the possibility of water intoxication and hyponatremia.

Post Marketing

There have been rare reports of thrombotic events (acute cerebrovascular thrombosis, acute myocardial infarction) following desmopressin acetate injection in patients predisposed to thrombus formation, and rare reports of hyponatremic convulsions associated with concomitant use with the following medications: oxybutinin and imipramine.

OVERDOSAGE

Signs of overdose may include confusion, drowsiness, continuing headache, problems with passing urine and rapid weight gain due to fluid retention. (See WARNINGS.) In case of overdosage, the dosage should be reduced, frequency of administration decreased, or the drug withdrawn according to the severity of the condition.
There is no known specific antidote for desmopressin acetate or desmopressin acetate injection 4 mcg/mL.
An oral LD50 has not been established. An intravenous dose of 2 mg/kg in mice demonstrated no effect.

DOSAGE AND ADMINISTRATION

Hemophilia A and von Willebrand’s Disease (Type I): Desmopressin acetate injection 4 mcg/mL is administered as an intravenous infusion at a dose of 0.3 mcg desmopressin acetate/kg body weight diluted in sterile physiological saline and infused slowly over 15 to 30 minutes. In adults and children weighing more than 10 kg, 50 mL of diluent is recommended; in children weighing 10 kg or less, 10 mL of diluent is recommended. Blood pressure and pulse should be monitored during infusion. If desmopressin acetate injection 4 mcg/mL is used preoperatively, it should be administered 30 minutes prior to the scheduled procedure.
The necessity for repeat administration of desmopressin acetate injection or use of any blood products for hemostasis should be determined by laboratory response as well as the clinical condition of the patient. The tendency toward tachyphylaxis (lessening of response) with repeated administration given more frequently than every 48 hours should be considered in treating each patient.
Fluid restriction should be observed. (See WARNINGS, PRECAUTIONS, Pediatric Use and Geriatric Use.)
Diabetes Insipidus: This formulation is administered subcutaneously or by direct intravenous injection. Desmopressin acetate injection 4 mcg/mL dosage must be determined for each patient and adjusted according to the pattern of response. Response should be estimated by two parameters: adequate duration of sleep and adequate, not excessive, water turnover.
The usual dosage range in adults is 0.5 mL (2 mcg) to 1 mL (4 mcg) daily, administered intravenously or subcutaneously, usually in two divided doses. The morning and evening doses should be separately adjusted for an adequate diurnal rhythm of water turnover. For patients who have been controlled on intranasal desmopressin acetate and who must be switched to the injection form, either because of poor intranasal absorption or because of the need for surgery, the comparable antidiuretic dose of the injection is about one-tenth the intranasal dose.
Fluid restriction should be observed. (See WARNINGS, PRECAUTIONS, Pediatric Use and Geriatric Use.)
Parenteral drug products should be inspected visually for particulate matter and discoloration prior to administration whenever solution and container permit.
Geriatric Use: This drug is known to be substantially excreted by the kidney, and the risk of toxic reactions to this drug may be greater in patients with impaired renal function. Because elderly patients are more likely to have decreased renal function, care should be taken in dose selection, and it may be useful to monitor renal function. (See CLINICAL PHARMACOLOGY, Human Pharmacokinetics, CONTRAINDICATIONS, and PRECAUTIONS, Geriatric Use.)

HOW SUPPLIED

Desmopressin acetate injection, USP 4 mcg/mL is available as a sterile solution in 10 mL multiple-dose vials (NDC 62756-529-26), each containing 4 mcg desmopressin acetate, USP per mL.
Store refrigerated 2° to 8°C (36° to 46°F). Preserve in tight containers, protected from light.
Keep out of the reach of children.
Distributed by:
Sun Pharmaceutical Industries, Inc.
Cranbury, NJ 08512
Manufactured by:
Sun Pharmaceutical Ind. Ltd.
Halol-Baroda Highway,
Halol-389 350, Gujarat, India.
ISS. 12/2014
PJPI0435A

PRINCIPAL DISPLAY PANEL

NDC 62756-529-26
Rx only
Desmopressin Acetate Injection, USP
FOR INTRAVENOUS/SUBCUTANEOUS USE ONLY
One 10 mL Multiple-dose Vial
Refrigerate
40 mcg/10 mL (4 mcg/mL)
NOVAPLUS
SUN PHARMA